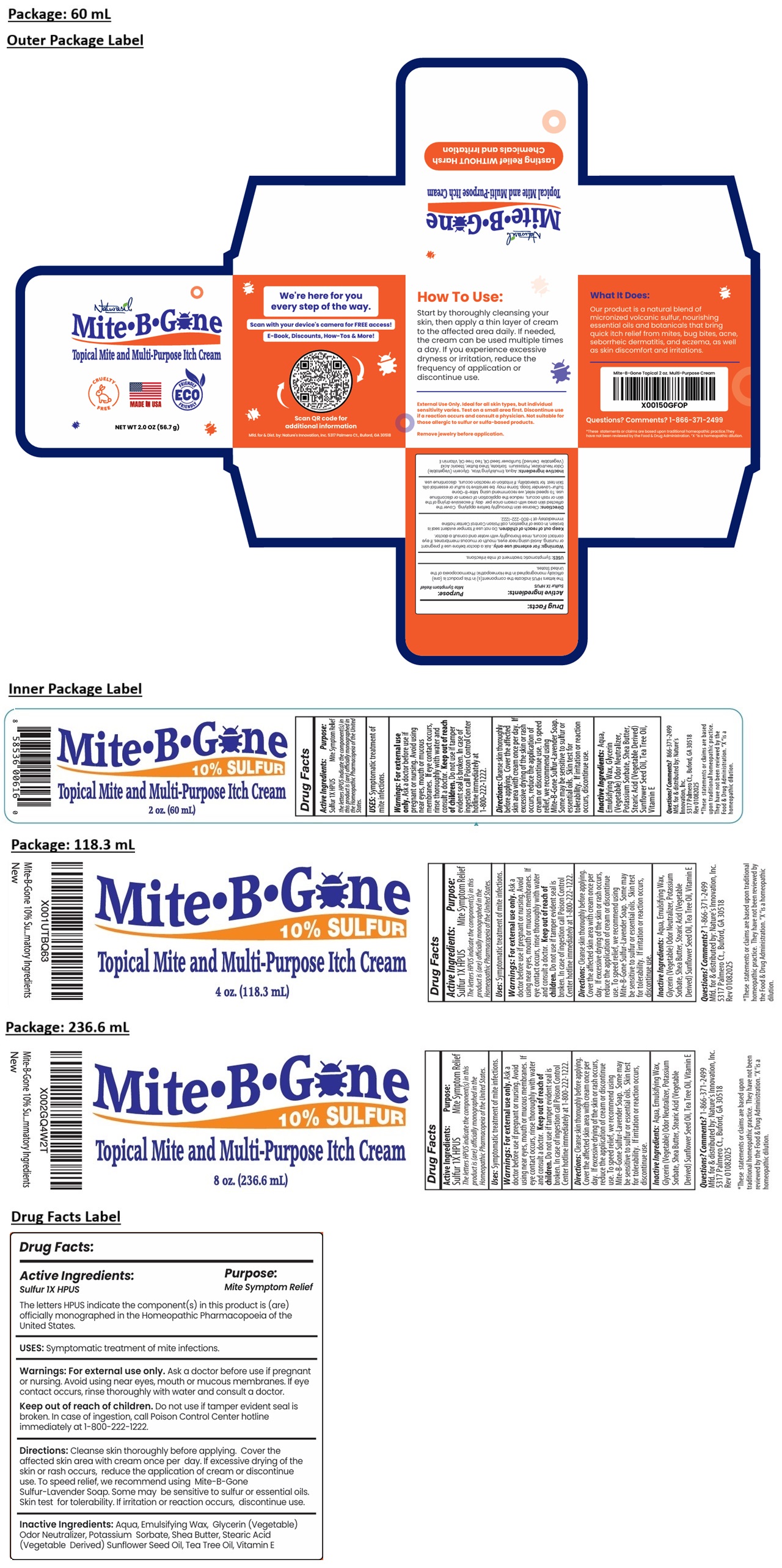 DRUG LABEL: Naturasil
NDC: 10893-430 | Form: CREAM
Manufacturer: Nature's Innovation, Inc
Category: homeopathic | Type: HUMAN OTC DRUG LABEL
Date: 20251009

ACTIVE INGREDIENTS: SULFUR 0.1 g/100 mL
INACTIVE INGREDIENTS: WATER; ETHYLENE DISTEARAMIDE; GLYCERIN; POTASSIUM SORBATE; SHEA BUTTER; STEARIC ACID; SUNFLOWER OIL; TEA TREE OIL; .ALPHA.-TOCOPHEROL

Mite• B• Gone Topical Mite and Multi-Purpose Itch Cream

Active Ingredients:

Sulfur 1X HPUS

The letters HPUS indicate the component(s) in this product is (are) officially monographed in the Homeopathic Pharmacopeia of the United States.

Purpose:

Mite Symptom Relief

USES:

Symptomatic treatment of mite infections.

Warnings:

For external use only. Ask a doctor before use if pregnant or nursing. Avoid using near eyes, mouth or mucous membranes. If eye contact occurs, rinse thoroughly with water and consult a doctor.

Keep out of reach of children. Do not use if tamper evident seal is broken. In case of ingestion, call Poison Control Center hotline immediately at 1-800-222-1222.

Directions:

Cleanse skin thoroughly before applying. Cover the affected skin area with cream once per day. If excessive drying of the skin or rash occurs, reduce the application of cream or discontinue use. To speed relief, we recommend using Mite-B-Gone Sulfur-Lavender Soap. Some may be sensitive to sulfur or essential oils. Skin test for tolerability. If irritation or reaction occurs, discontinue use.

Inactive Ingredients:

Aqua, Emulsifying Wax, Glycerin (Vegetable), Odor Neutralizer, Potassium Sorbate, Shea Butter, Stearic Acid (Vegetable Derived), Sunflower Seed Oil, Tea Tree Oil, Vitamin E

Questions? Comments?

1-866-371-2499

Topical Mite and Multi-Purpose Itch Cream

CRUELTY FREE

MADE IN USA

ECO FRIENDLY

We're here for you every step of the way.

Scan with your device's camera for FREE access!
E-Book, Discounts, How-Tos & More!

Scan QR code for
additional information

Mfd. for & Dist. by. Nature's Innovation, Inc. 5317 Palmero Ct., Buford, GA 30518

How To Use:
Start by thoroughly cleansing your skin, then apply a thin layer of cream to the affected area daily. If needed, the cream can be used multiple times a day. If you experience excessive dryness or irritation, reduce the frequency of application or discontinue use.

External Use Only. Ideal for all skin types, but individual sensitivity varies. Test on a small area first. Discontinue use if a reaction occurs and consult a physician. Not suitable for those allergic to sulfur or sulfa-based products.

Remove jewelry before application.

What It Does:

Our product is a natural blend of micronized volcanic sulfur, nourishing essential oils and botanicals that bring quick itch relief from mites, bug bites, acne, seborrheic dermatitis, and eczema, as well as skin discomfort and irritations.

*These statements or claims are based upon traditional homeopathic practice. They have not been reviewed by the Food & Drug Administration. “X“ is a homeopathic dilution.

10% SULFUR